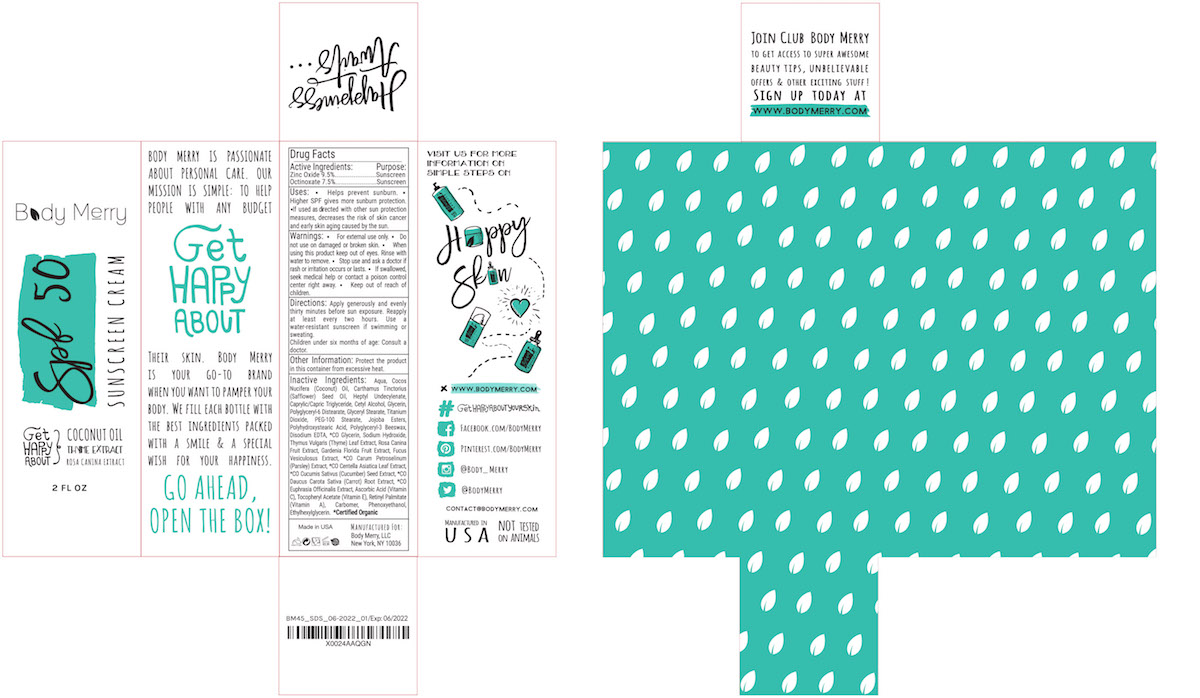 DRUG LABEL: Body Merry SPF 15 Sunscreen Cream
NDC: 73428-1002 | Form: LOTION
Manufacturer: Body Merry, LLC
Category: otc | Type: HUMAN OTC DRUG LABEL
Date: 20210115

ACTIVE INGREDIENTS: ZINC OXIDE 0.095 mg/1 mL; OCTINOXATE 0.075 mg/1 mL
INACTIVE INGREDIENTS: MEDIUM-CHAIN TRIGLYCERIDES; WATER; COCONUT OIL; SAFFLOWER OIL; CETYL ALCOHOL; GLYCERIN

Body Merry SPF 50 Sunscreen Cream

Active Ingredients

Octinoxate 7.5%

Zinc Oxide 9.5%

Purpose

Sunscreen

Warnings

- For external use only.
- Do not use on broken or damaged skin
- When using this product, keep out of eyes. Rinse with water to remove.
- Stop use and ask a doctor is rash or irritation occurs or lasts.
- If swallowed, seek medical help or contact a poison control center right away.
- Keep out of reach of children.

Directions

Apply every morning as a daily moisturizer. Apply generously and evenly 15 minutes before sun exposure. Reapply at least every two hours. Use a water-resistant sunscreen if swimming or sweating. Children under six months of age: consult a doctor before use.

Other Information

Protect the product in this container from excessive heat.

Uses:

Helps prevent sunburn. Higher SPF gives more sunburn protection. If used as directed with other sun protection measures (see Sun Alert) decreases the risk of skin cancer and early skin aging caused by the sun.

Sun Alert: Spending time in the use increases your risk of skin cancer and early skin aging. To decrease this risk, regularly use a sunscreen with a broad-spectrum SPF value of 15 or higher and other sun protection measures such as limited time in the sun, especially from 10 a.m. to 2 p.m. Wear long pants, hats, sunglasses, and long-sleeve shirts.

Inactive Ingredients:

Water, Cocos Nucifera (Coconut) Oil, Carthamus Tinctorius (Safflower) Seed Oil, Cetyl Alcohol, Caprylic/Capric Triglyceride, Glycerin, Glyceryl Stearate, PEG-100 Stearate, Titanium Dioxide, Polyglyceryl-3 Beeswax, Polyglyceryl-6 Distearate, Jojoba Esters, Polyhydroxystearic Acid, Carbomer, *CO Glycerin, Sodium Hydroxide, Thymus Vulgaris (Thyme) Leaf Extract, Rosa Canina Fruit Extract, Gardenia Florida Fruit Extract, Fucus Vesiculosus Extract, *CO Carum Petroselinum (Parsley) Extract, *CO Centella Asiatica Leaf Extract, *CO Cucumis Sativus (Cucumber) Seed Extract, *CO Daucus Carota Sativa (Carrot) Root Extract, *CO Euphrasia Officinalis Extract, Benzyl Alcohol, Disodium EDTA, Dehydroacetic Acid

Warning

Keep out of reach of children.